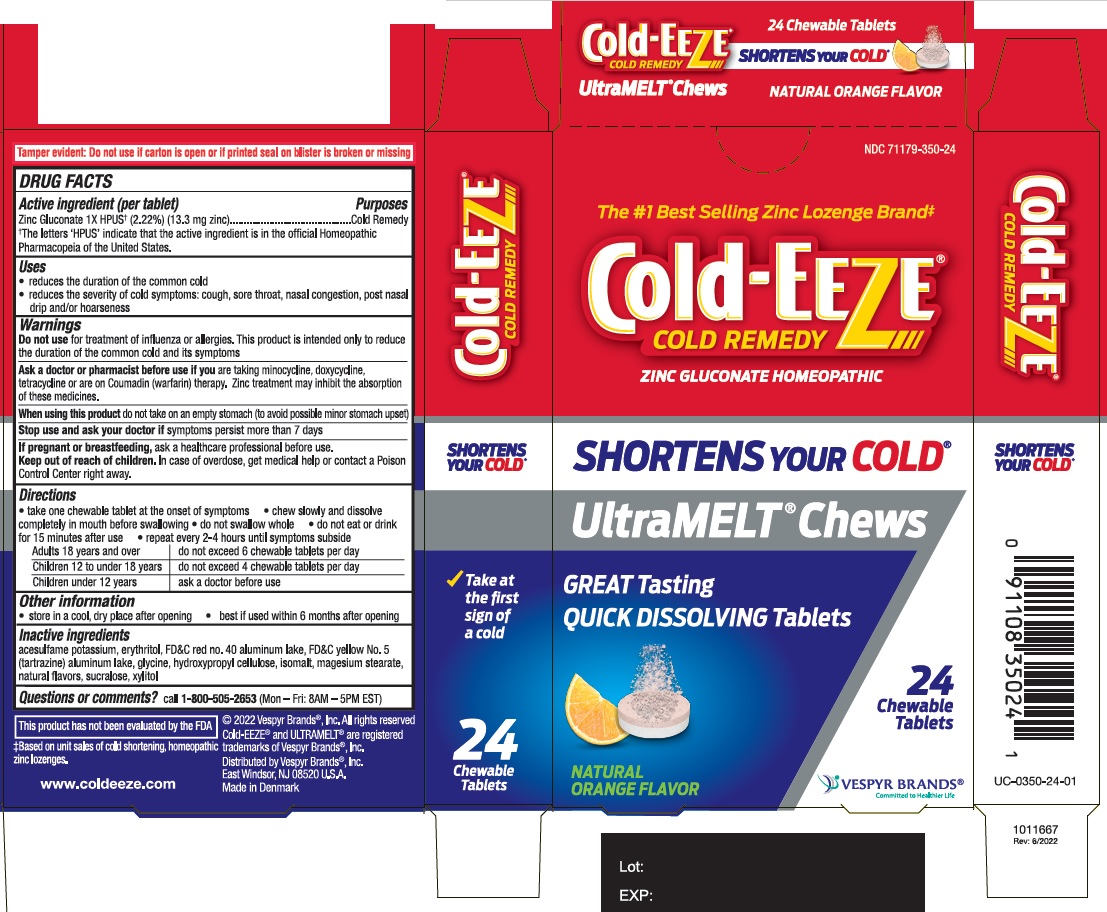 DRUG LABEL: Cold-EEZE Cold Remedy
NDC: 71179-350 | Form: TABLET, CHEWABLE
Manufacturer: Vespyr Brands Inc
Category: homeopathic | Type: HUMAN OTC DRUG LABEL
Date: 20250101

ACTIVE INGREDIENTS: ZINC GLUCONATE 13.3 mg/1 1
INACTIVE INGREDIENTS: GLYCINE; SUCRALOSE; ACESULFAME POTASSIUM; XYLITOL; HYDROXYPROPYL CELLULOSE, UNSPECIFIED; MAGNESIUM STEARATE; ISOMALT; FD&C YELLOW NO. 5 ALUMINUM LAKE; ERYTHRITOL; FD&C RED NO. 40

Cold-EEZE Cold Remedy UltraMELT Chews

Active ingredient

Active ingredient (per tablet)
Zinc Gluconate 1X HPUS† (2.22%) (13.3 mg zinc)
† The letters ‘HPUS’ indicate that the active ingredient is in the official Homeopathic Pharmacopeia of the United States.

Purposes

Cold remedy

Uses

- reduces the duration of the common cold
- reduces the severity of cold symptoms: cough, sore throat, nasal congestion, post nasal drip and/or hoarseness

Warnings

Do not use for treatment of influenza or allergies. This product is intended only to reduce the duration of the common cold and its symptoms.

Ask a doctor or pharmacist before use if you are taking minocycline, doxycycline, tetracycline or are on Coumadin (warfarin) therapy. Zinc treatment may inhibit the absorption of these medicines.

When using this product do not take on an empty stomach (to avoid possible minor stomach upset)

Stop use and ask your doctor if symptoms persist more than 7 days

PREGNANCY OR BREAST FEEDING

If pregnant or breastfeeding, ask a healthcare professional before use.

Keep out of reach of children. In case of overdose, get medical help or contact a Poison Control Center right away.

Directions

• take one chewable tablet at the onset of symptoms • chew slowly and dissolve completely in mouth before swallowing
• do not swallow whole • do not eat or drink for 15 minutes after use • repeat every 2-4 hours until symptoms subside

Adults 18 years and over | do not exceed 6 chewable tablets per day
Children 12 to under 18 years | do not exceed 4 chewable tablets per day
Children under 12 years | ask a doctor before use

Other information

- store in a cool, dry place after opening
- best if used within 6 months after opening

Inactive ingredients

acesulfame potassium, erythritol, FD&C red no. 40 aluminum lake, FD&C yellow No. 5 (tartrazine) aluminum lake, glycine, hydroxypropyl cellulose, isomalt, magnesium stearate, natural flavors, sucarlose, xylitol

Questions?

call 1-800-505-2653 (Mon – Fri: 8AM – 5PM EST)

PACKAGE LABEL

Cold-EEZE®

COLD REMEDY

ZINC GLUCONATE HOMEOPATHIC

SHORTENS YOUR COLD®

UltraMELT® Chews

GREAT Tasting

QUICK DISSOLVING Tablets

NATURAL ORANGE FLAVOR

24 Chewable Tablets

©2022 Vespyr Brands®, Inc.

Cold-EEZE® and ULTRAMELT® are registered trademarks of Vespyr Brands®, Inc.

Distributed by Vespyr Brands®, Inc.

East Windsor, NJ 08520 USA

This product has not been evaluated by the FDA

Made in Denmark

www.coldeeze.com